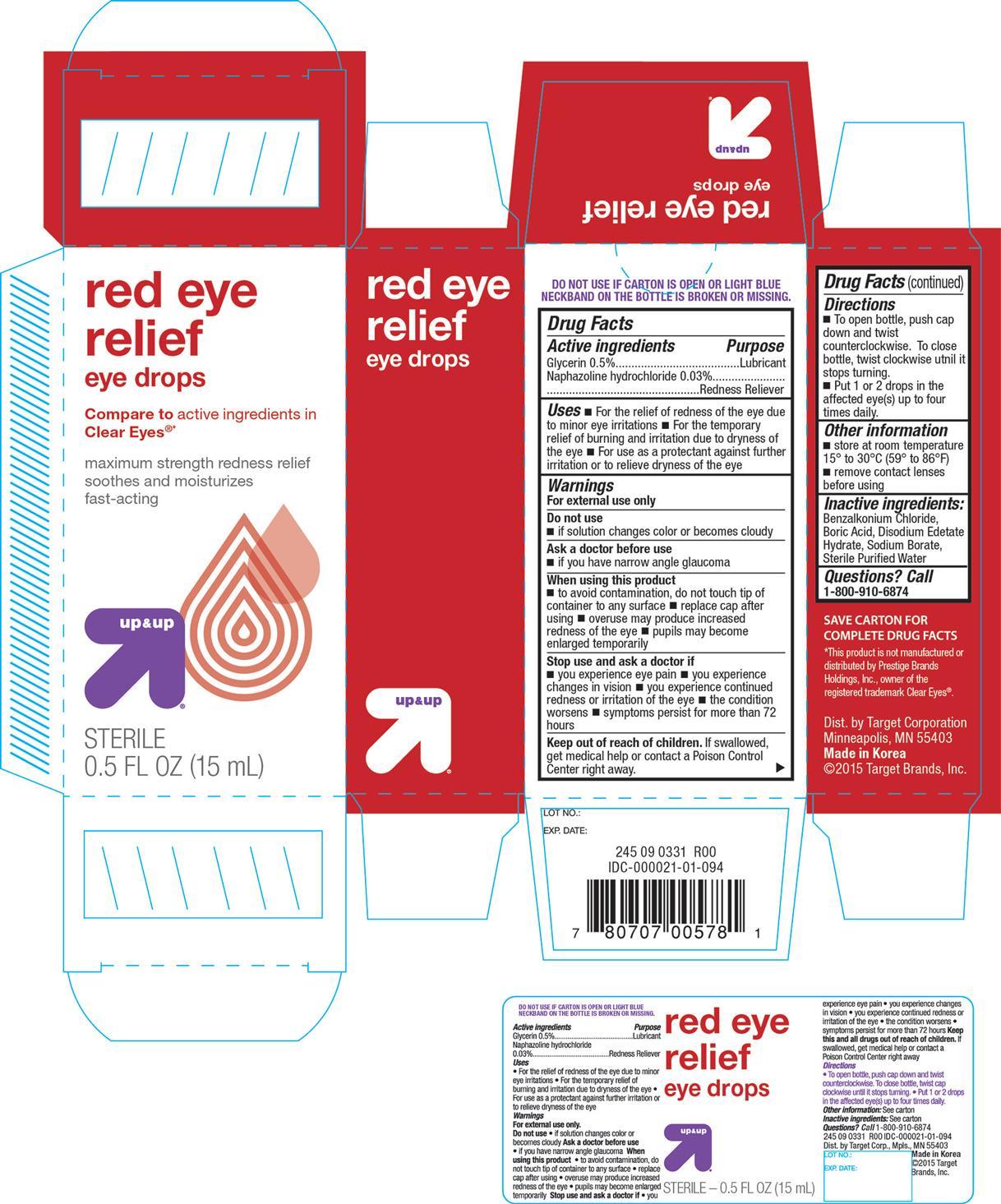 DRUG LABEL: Red Eye Relief
NDC: 11673-578 | Form: SOLUTION/ DROPS
Manufacturer: Target Corporation
Category: otc | Type: HUMAN OTC DRUG LABEL
Date: 20150304

ACTIVE INGREDIENTS: GLYCERIN 500 mg/100 mL; NAPHAZOLINE HYDROCHLORIDE 30 mg/100 mL
INACTIVE INGREDIENTS: BENZALKONIUM CHLORIDE; BORIC ACID; SODIUM BORATE; WATER

Active ingredients Purpose

Glycerin 0.5%................................................... Lubricant

Naphazoline hydrochloride 0.33%........................ Redness Reliever

Uses

- For the relief of redness of the eye due to minor eye irritations
- For the temporary relief of burning and irritation due to dryness of the eye
- For use as a protectant against futher irritation or to relive dryness of the eye

Warnings

For external use only

Do not use

- if solution changes color or becomes cloudy

Ask a doctor before use

- if you have narrow angle glaucoma

When using this product

- to avoid contamination, do not touch tip of container to any surface
- replace cap after using
- overuse may product icreased redness of the eye
- pupils may become enlarged temporarily

Stop use and ask a doctor if

- you experience eye pain
- you experience changes in vision
- you experience continued redness of the eye
- pupils may become enlarged temporarily

Stop use and ask a doctor if

- you experience eye pain
- you experience changes in vision
- you experience continued redness or irritation of the eye
- the condition worsens
- symptoms persist for more than 72 hours

Keep out of reach of children. If swallowed, get medical help or contact a Poison Control Center right away

Directions

- To open bottle, push cap down and twist counterclockwise. To close bottle, twist clockwise until it stops turning

Inactive ingredients:

Benzalkonium Choride, Boric Acid, Disodium Edetate Hydrate, Sodium Borate, Sterile Purified Water

DOSAGE AND ADMINISTRATION

DISTRIBUTED BY:

TARGET CORPORATION

MINNEAPOLIS, MN 55403

MADE IN KOREA